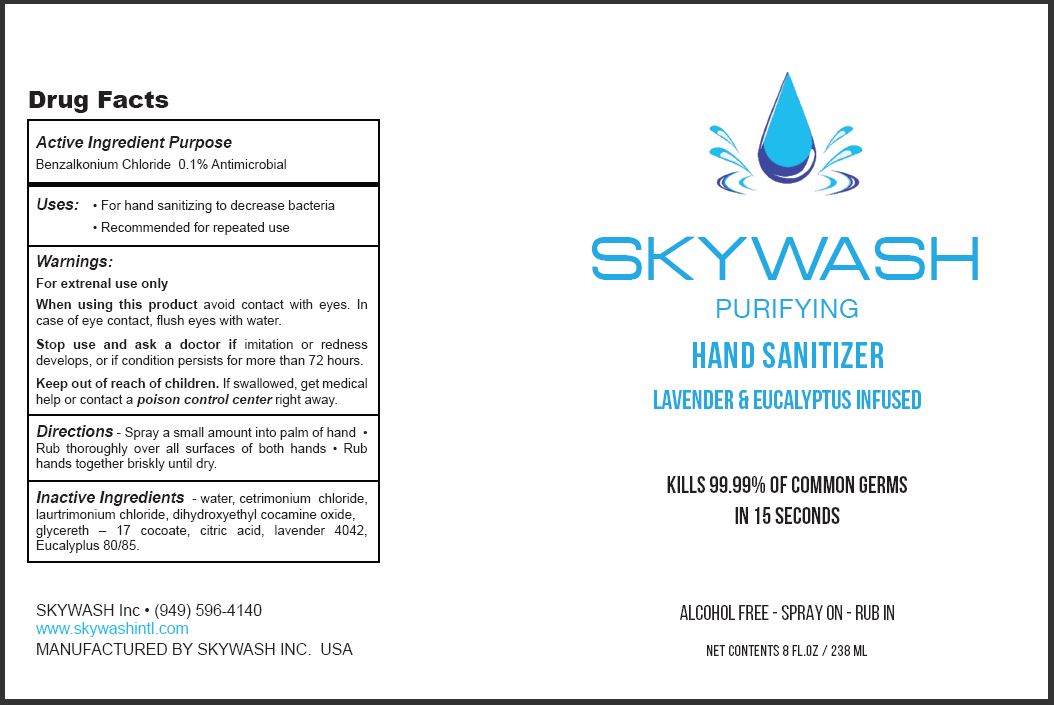 DRUG LABEL: HAND SANITIZER
NDC: 78987-101 | Form: SPRAY
Manufacturer: Skywash International
Category: otc | Type: HUMAN OTC DRUG LABEL
Date: 20210922

ACTIVE INGREDIENTS: BENZALKONIUM CHLORIDE 0.1 g/100 mL
INACTIVE INGREDIENTS: WATER; CETRIMONIUM CHLORIDE; LAURTRIMONIUM CHLORIDE; DIHYDROXYETHYL COCAMINE OXIDE; GLYCERETH-17 COCOATE; ANHYDROUS CITRIC ACID; LAVENDER OIL; EUCALYPTUS OIL

SKYWASH - PURIFYING HAND SANITIZER - 0.1% BKC

ACTIVE INGREDIENT

BENZALKONIUM CHLORIDE 0.1%

PURPOSE

ANTIMICROBIAL

USES

- For hand sanitizing to decrease bacteria
- Recommended for repeated use

WARNINGS

For extrenal use only

When using this product avoid contact with eyes. In case of eye contact, flush eyes with water.

Stop use and ask a doctor if imitation or redness develops, or if condition persists for more than 72 hours.

Keep out of reach of children.

If swallowed, get medical help or contact a poison control center right away.

DIRECTIONS

Spray a small amount into palm of hand

- Rub thoroughly over all surfaces of both hands
- Rub hands together briskly until dry.

INACTIVE INGREDIENTS

water, cetrimonium chloride, laurtrimonium chloride, dihydroxyethyl cocamine oxide, glycereth–17 cocoate, citric acid, lavender 4042, Eucalyplus 80/85.